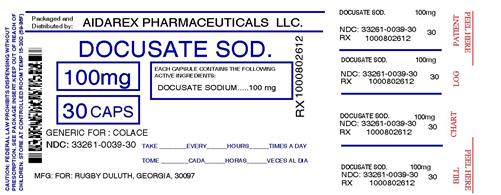 DRUG LABEL: Non-Habit Forming Stool Softener
NDC: 33261-039 | Form: CAPSULE, LIQUID FILLED
Manufacturer: Aidarex Pharmaceuticals LLC
Category: otc | Type: HUMAN OTC DRUG LABEL
Date: 20121005

ACTIVE INGREDIENTS: DOCUSATE SODIUM 100 mg/1 1
INACTIVE INGREDIENTS: FD&C RED NO. 40; FD&C YELLOW NO. 6; GELATIN; GLYCERIN; POLYETHYLENE GLYCOLS; PROPYLENE GLYCOL; WATER; SORBITOL

Non-Habit Forming Stool Softener Laxative

Active Ingredient (in each softgel capsule)

Docusate Sodium 100mg

Purpose

Stool softener

Uses

- Relieves occasional constipation.
- Generally produces bowel movement within 12 to72 hours.

Warnings - Do not use

- for longer than one week
- if you are taking mineral oil
- when abdominal pain, nausea, or vomiting are present

Ask a doctor before use if

you have a sudden change in bowel habits that lasts over two weeks

Ask a doctor or pharmacist before use if you are taking any other drug. Take this product two or more hours before or after other drugs. Laxatives may affect how other drugs work.

Stop use and ask a doctor if

- you experience rectal bleeding
- you fail to have a bowel movement after using this product

These may indicate a serious condition.

If pregnant or breastfeeding

ask a health professional before use.

Keep out of reach of children.

In case of overdose, get medical help or contact a Poison Control Center right away.

Directions

- adults and children over 12 years and over:1 capsule once daily or in divided doses
- children 6 to under 12 years: 1 capsule once daily
- children under 6 years: ask a doctor

Other information

- store at controlled room temperature 15 - 30 degrees C (59-86 degrees F)

Each capsule contains sodium 6mg

Inactive Ingredients

edible white ink, FDandC Red No. 40, FDandC Yellow No. 6, gelatin, glycerin, polyethylene glycol, propylene glycol, purified water, sorbitol special.

Questions or comments?

Call 1-800-645-2158, 9am - 5am ET Monday - Friday

Product Labeling

Rugby Extra Strength Stool Softener Laxative
Docusate Sodium USP, 250mg

*Rugby Laboratories, Inc is not affiliated with the ower of the trademark Colace(r).

Rugby stool softener Laxative is distributed by Rugby Laboratories, Inc.
Mfd for: Rugby Laboratories, Inc
Duluth Georgia 30097
www.rugbylaboratories.com

Repackaged By:
Aidarex Pharmaceuticals, LLC.
Corona, CA 92880